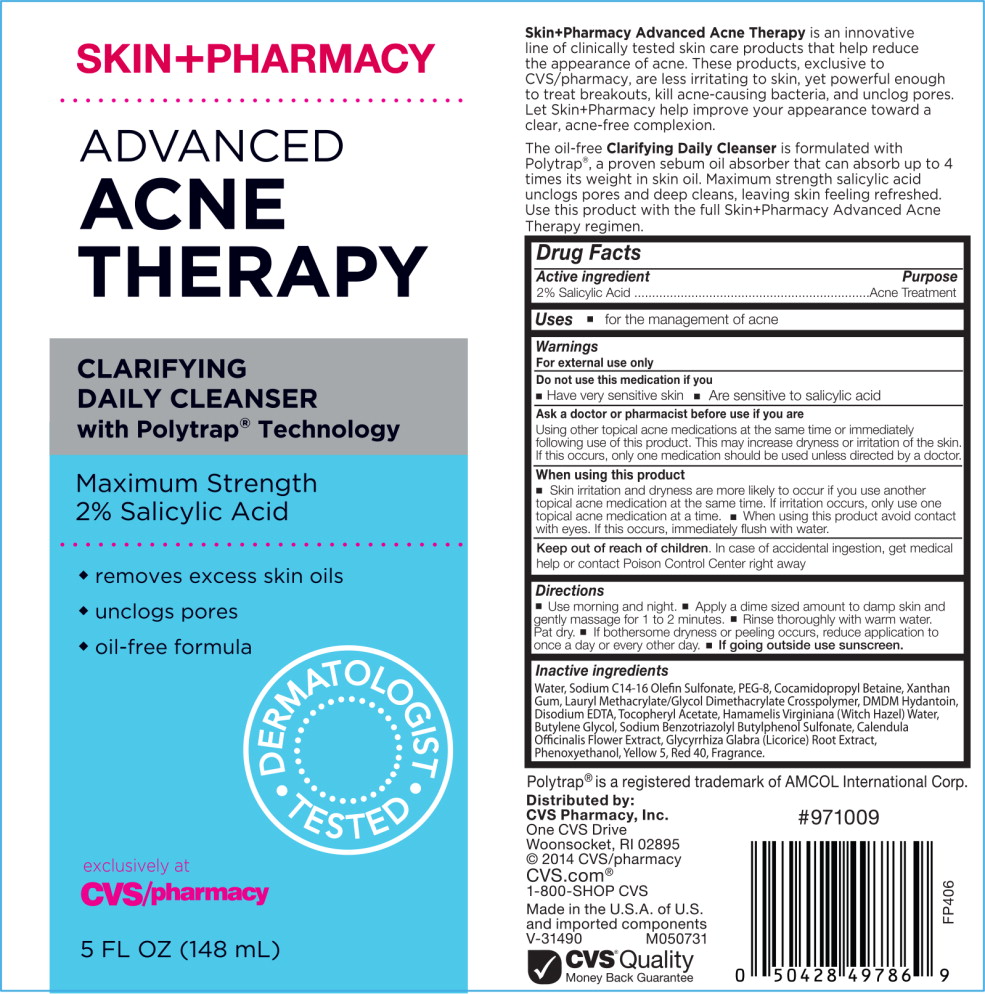 DRUG LABEL: SKIN PHARMACY ADVANCED ACNE THERAPY CLARIFYING DAILY CLEANSER
NDC: 69842-064 | Form: LIQUID
Manufacturer: CVS Health
Category: otc | Type: HUMAN OTC DRUG LABEL
Date: 20170223

ACTIVE INGREDIENTS: salicylic acid 20 mg/1 mL
INACTIVE INGREDIENTS: Water; sodium C14-16 olefin sulfonate; polyethylene glycol 4000; cocamidopropyl betaine; Xanthan gum; DMDM Hydantoin; edetate disodium; .alpha.-tocopherol acetate, DL-; Hamamelis virginiana flower water; Butylene glycol; Calendula Officinalis flower; licorice; Phenoxyethanol; FD&C Yellow No. 5; FD&C red no. 40; Lauryl Methacrylate/Glycol Dimethacrylate Crosspolymer

Drug Facts

Active Ingredient

2% Salicylic Acid

Purpose

Acne

INDICATIONS AND USAGE

Uses for the management of acne

Warnings

For external use only

Do not use this medication if you

- Have very sensitive skin
- Are sensitive to salicylic acid

Ask a doctor or pharmacist before use if you are

Using other topical acne medications at the same time or immediately following use of this product. This may increase dryness or irritation of the skin. If this occurs, only one medication should be used unless directed by a doctor.

When using this product

- Skin irritation and dryness are more likely to occur if you use another topical acne medication at the same time. If irritation occurs, only use one topical acne medication at the same time.
- When using this product avoid contact with eyes. If this occurs, immediately flush with water.

Keep out of reach of children. In case of accidental ingestion, get medical help or contact Poison Control Center right away.

Directions

- Use morning and night.
- Apply a dime sized amount to damp skin and gently massage for 1 to 2 minutes.
- Rinse thoroughly with warm water. Pat dry.
- If bothersome dryness or peeling occurs, reduce application to once a day or every other day.
- If going outside use sunscreen.

Inactive ingredients

Water, Sodium C14-16 Olefin Sulfonate, PEG-8, Cocamidopropyl Betaine, Xanthan Gum, Lauryl Methacrylate/Glycol Dimethacrylate Crosspolymer, DMDM Hydantoin, Disodium EDTA, Tocopheryl Acetate, Hamamelis Virginiana (Witch Hazel) Water, Butylene Glycol, Sodium Benzotriazolyl Butylphenol Sulfonate, Calendula Officinalis Flower Extract, Glycyrrhiza Glabra (Licorice) Root Extract, Phenoxyethanol, Yellow 5, Red 40, Fragrance.

Polytrap® is a registered trademark of AMCOL International Corp.

Save carton for complete labeling since all warnings are not included on the inner package.

Distributed by: CVS Pharmacy, Inc.
One CVS Drive, Woonsocket, RI 02895
© 2014 CVS/pharmacy

CVS.com® 1-800-SHOP CVS

Made in the U.S.A. of U.S. and imported components
V-31490
M050731

CVS® Quality
Money Back Guarantee

#971009
FP406

Principal Display Panel - Bottle Label

SKIN+PHARMACY

ADVANCED
ACNE
THERAPY

CLARIFYING
DAILY CLEANSER
with Polytrap® Technology

Maximum Strength
2% Salicylic Acid

- removes excess skin oils
- unclogs pores
- oil-free formula

DERMATOLOGIST TESTED

exclusively at CVS/pharmacy

5 FL OZ (148 mL)